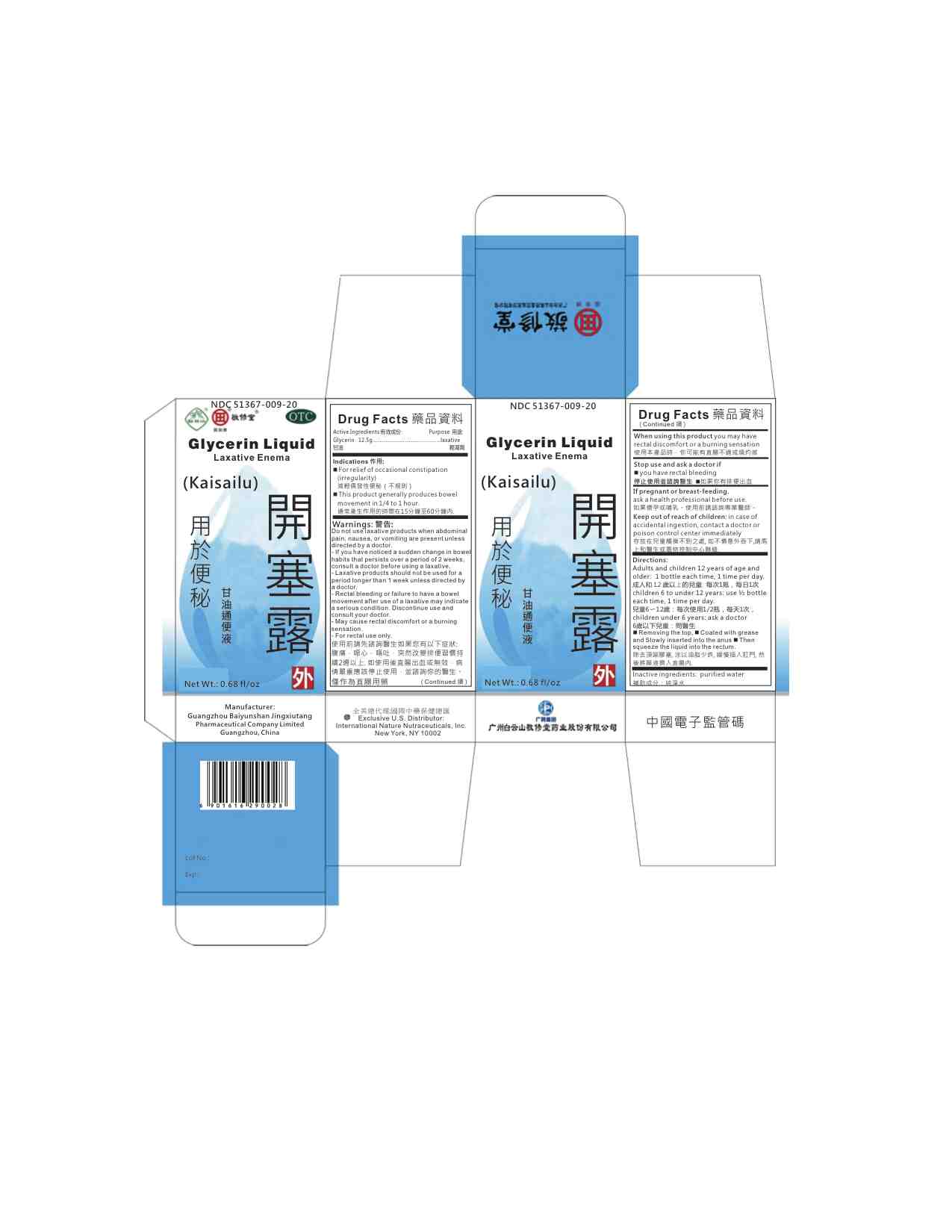 DRUG LABEL: Glycerin Liquid Laxative Enema(Kaisalilu)
NDC: 51367-009 | Form: LIQUID
Manufacturer: International Nature Nutraceuticals
Category: otc | Type: HUMAN OTC DRUG LABEL
Date: 20191226

ACTIVE INGREDIENTS: GLYCERIN 12.5 g/1 1
INACTIVE INGREDIENTS: WATER

Drug Facts

Active Ingredients

Glycerin- 12.5g

Indications

For relief of occasional constipation

(irregularity)

減輕偶發性便秘（不規則）

This product generally produces bowel

movement in 1/4 to 1 hour.

通常產生作用的時間在15分鐘至60分鐘內.

Warnings:

Do not use laxative products when abdominal

pain, nausea, or vomiting are present unless

directed by a doctor.

- If you have noticed a sudden change in bowel

habits that persists over a period of 2 weeks,

consult a doctor before using a laxative.

- Laxative products should not be used for a

period longer than 1 week unless directed by

a doctor.

- Rectal bleeding or failure to have a bowel

movement after use of a laxative may indicate

a serious condition. Discontinue use and

consult your doctor.

- May cause rectal discomfort or a burning

sensation.

- For rectal use only.

使用前請先諮詢醫生如果您有以下症狀:

腹痛，噁心，嘔吐，突然改變排便習慣持

續2週以上. 如使用後直腸出血或無效，病

情嚴重應該停止使用，並諮詢你的醫生。

僅作為直腸用藥

Keep out of reach of children

In case of accidental ingestion, contact doctor or a poision control center immediately

Stop use and ask doctor if:

you have rectal bleeding

停止使用並諮詢醫生 n如果你有排便出血

Do not use:

If pregnant or breast-feeding.

ask a health professional before use.

如果懷孕或哺乳。使用前請諮詢專業醫師。

Directions:

Adults and children 12 years of age and

older: 1 bottle each time, 1 time per day.

成人和 12 歲以上的兒童: 每次1瓶，每日1次

children 6 to under 12 years: use ½ bottle

each time, 1 time per day.

兒童6〜12歲：每次使用1/2瓶，每天1次，

children under 6 years: ask a doctor

6歲以下兒童：問醫生

Removing the top, Coated with grease

and Slowly inserted into the anus Then

squeeze the liquid into the rectum.

除去頂端膠塞, 涂以油脂少許, 緩慢插入肛門, 然

後將藥液擠入直腸內.

When using this product:

you may have rectal discomfort or a burning sensation

使用本產品時，你可能有直腸不適或燒灼感

Inactive Ingredients

Purified water 純淨水